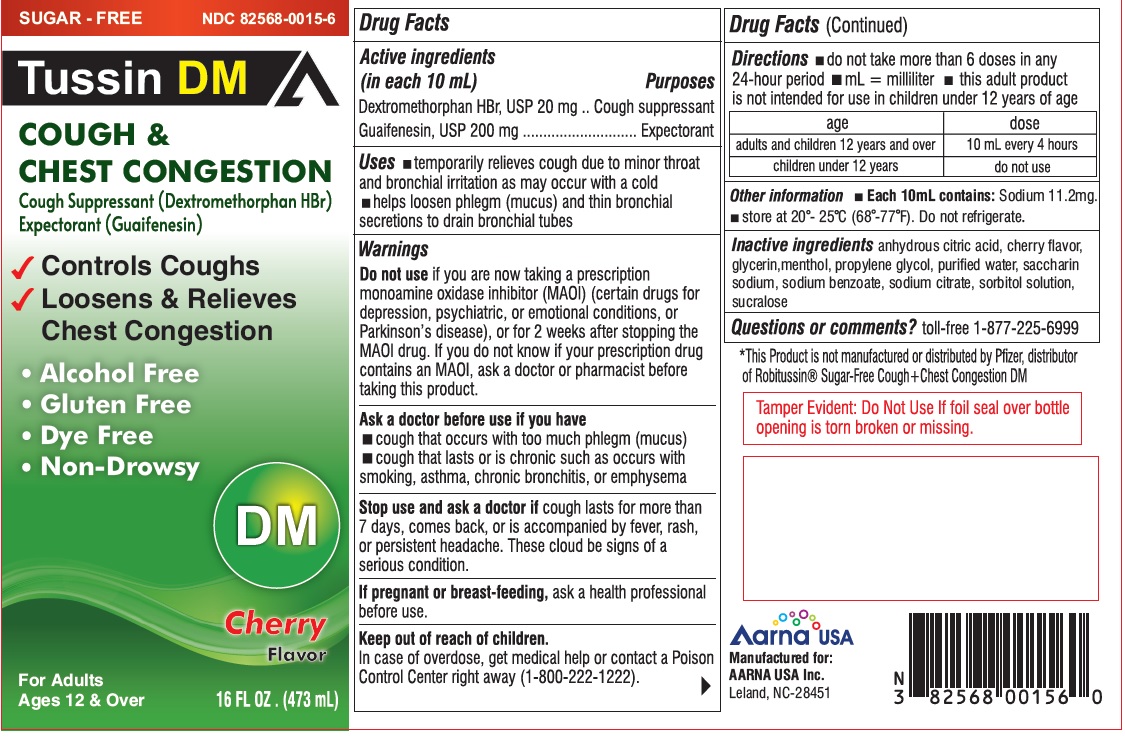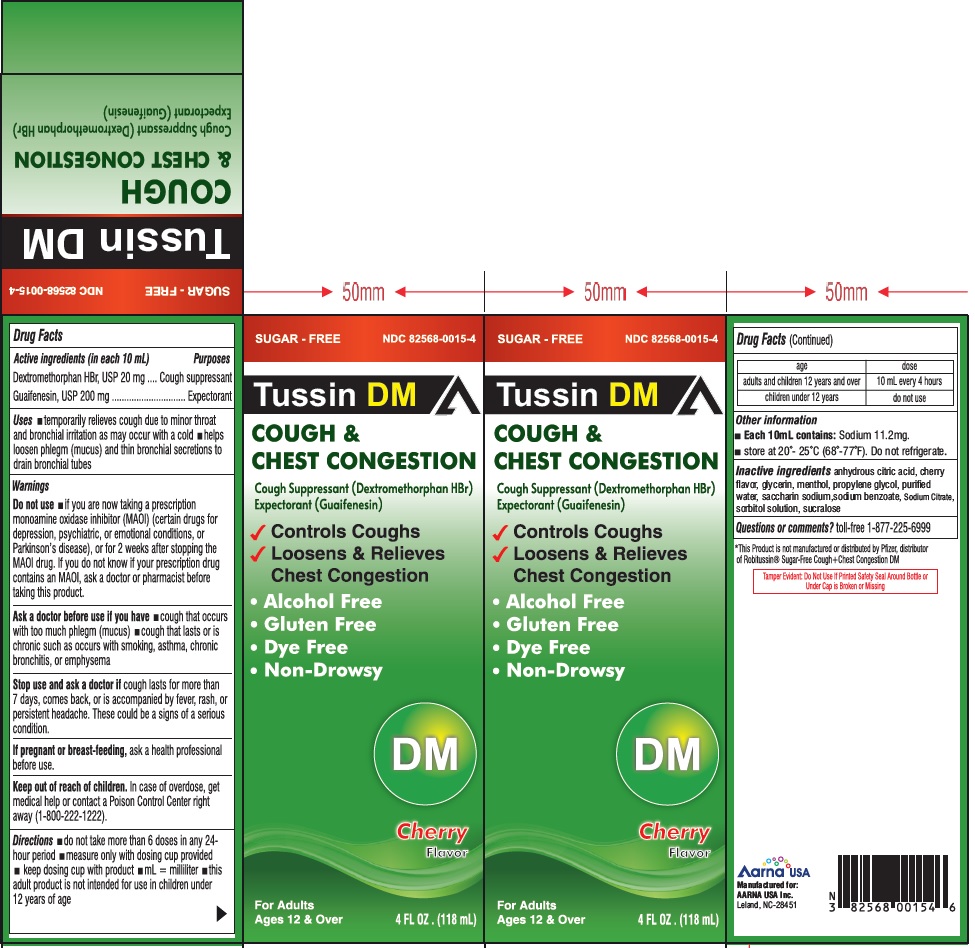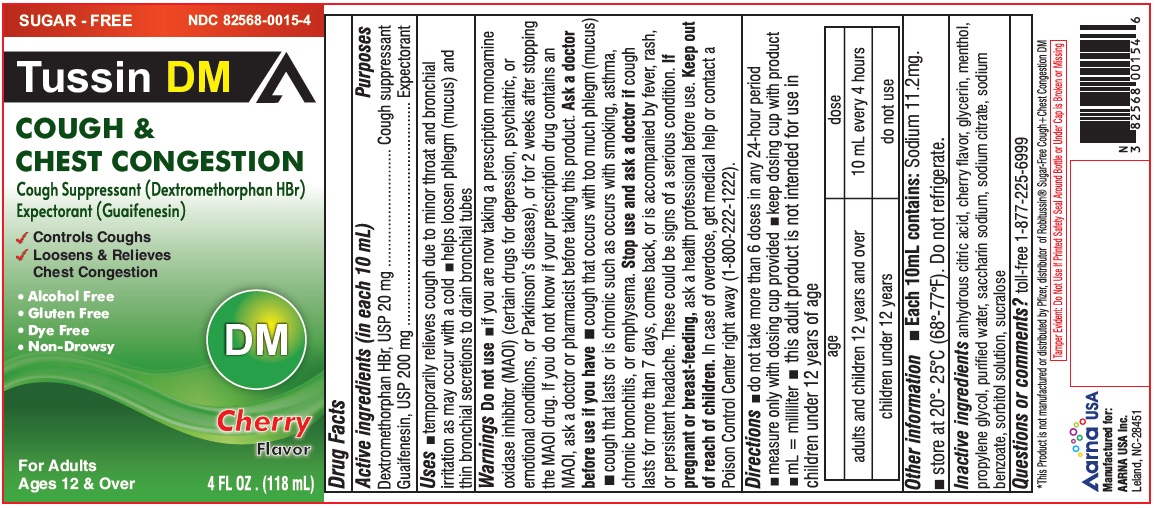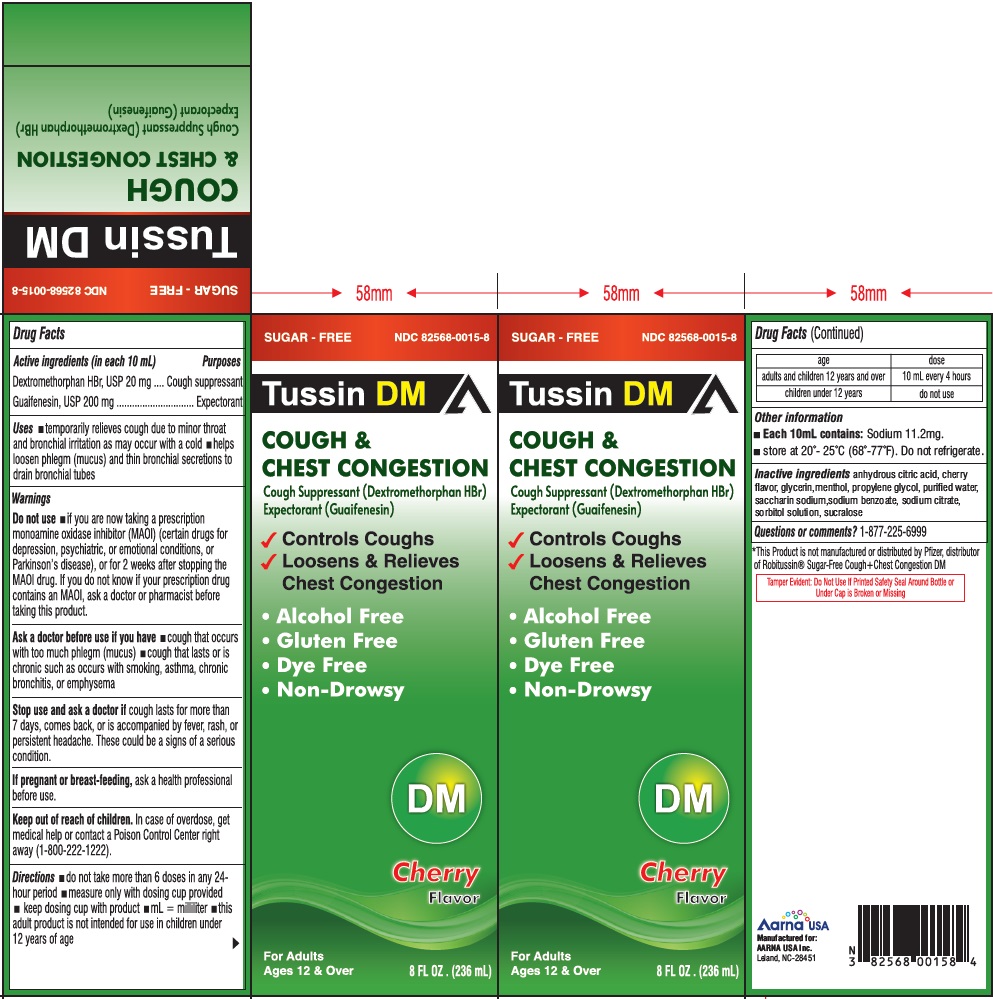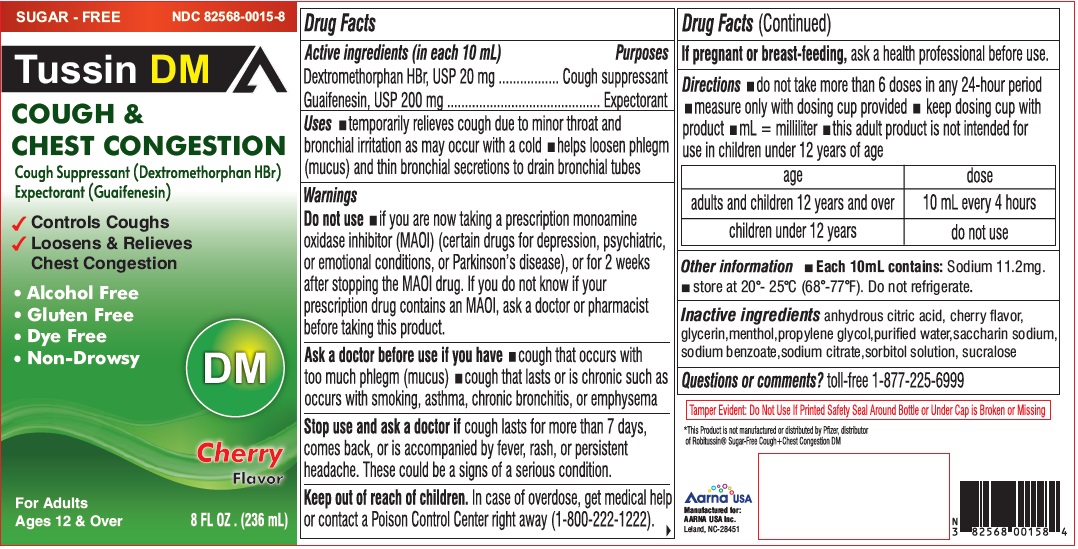 DRUG LABEL: Tussin DM Sugar free
NDC: 82568-0015 | Form: LIQUID
Manufacturer: AARNA USA, Inc.
Category: otc | Type: HUMAN OTC DRUG LABEL
Date: 20250516

ACTIVE INGREDIENTS: DEXTROMETHORPHAN HYDROBROMIDE 20 mg/10 mL; GUAIFENESIN 200 mg/10 mL
INACTIVE INGREDIENTS: ANHYDROUS CITRIC ACID; GLYCERIN; MENTHOL; PROPYLENE GLYCOL; WATER; SACCHARIN SODIUM; SODIUM BENZOATE; SODIUM CITRATE; SORBITOL SOLUTION; SUCRALOSE

TUSSIN DM Sugar Free
Cough and Chest Congestion
Cherry Flavor
Drug Facts

Active ingredient (in each 10 mL)

Dextromethorphan HBr, USP 20 mg

Guaifenesin, USP 200 mg

Purposes

Cough suppressant and Expectorant

Uses

- temporarily relieves cough due to minor throat and bronchial irrttation as may occur wtth a cold
- helps loosen phlegm (mucus) and thin bronchial secretions to drain bronchial tubes

Warnings

Do not use

if you are now taking a prescription monoamine oxidase inhibitor (MAOI) (certain drugs for depression, psychiatric, or emotional conditions, or
Parkinson's disease), or for 2 weeks after stopping the MAOI drug. tt you do not know tt your prescription drug contains an MAOI, ask a doctor or pharmacist before taking this product.

Ask a doctor before use if you have

- cough that occurs with too much phlegm (mucus)
- cough that lasts or is chronic such as occurs with smoking, asthma, chronic bronchitis or emphysema

Stop use and ask a doctor if

cough lasts more than 7 days, comes back, or is accompanied by fever, rash, or persistent headache. These could be signs of a serious condition.

If pregnant or breast-feeding,

ask a health professional before use.

Keep out of reach of children.

In case of overdose, get medical help or contact a Poison Control Center right away (1-800-222-1222).

Directions

- do not take more than 6 doses in any 24-hour period
- mL= milliliter
- this adult product is not intended for use in children under 12 years of age

age | dose
adults and children 12 years and over | 10 mL every 4 hours
children under 12 years | do not use

Other information

- Each 10 mL contains:Sodium 11.2 mg
- store between 20º-25ºC(68º-77ºF). Do not refrigerate.

Inactive ingredients

anhydrous citric acid, cherry flavor, glycerin, menthol, propylene glycol, purified water, saccharin sodium, sodium benzoate, sodium citrate, sorbitol solution, sucralose.

Questions or comments?

toll-free 1-877-225-6999

Manufactured for:

AARNA USA Inc.

Leland NC, 28451